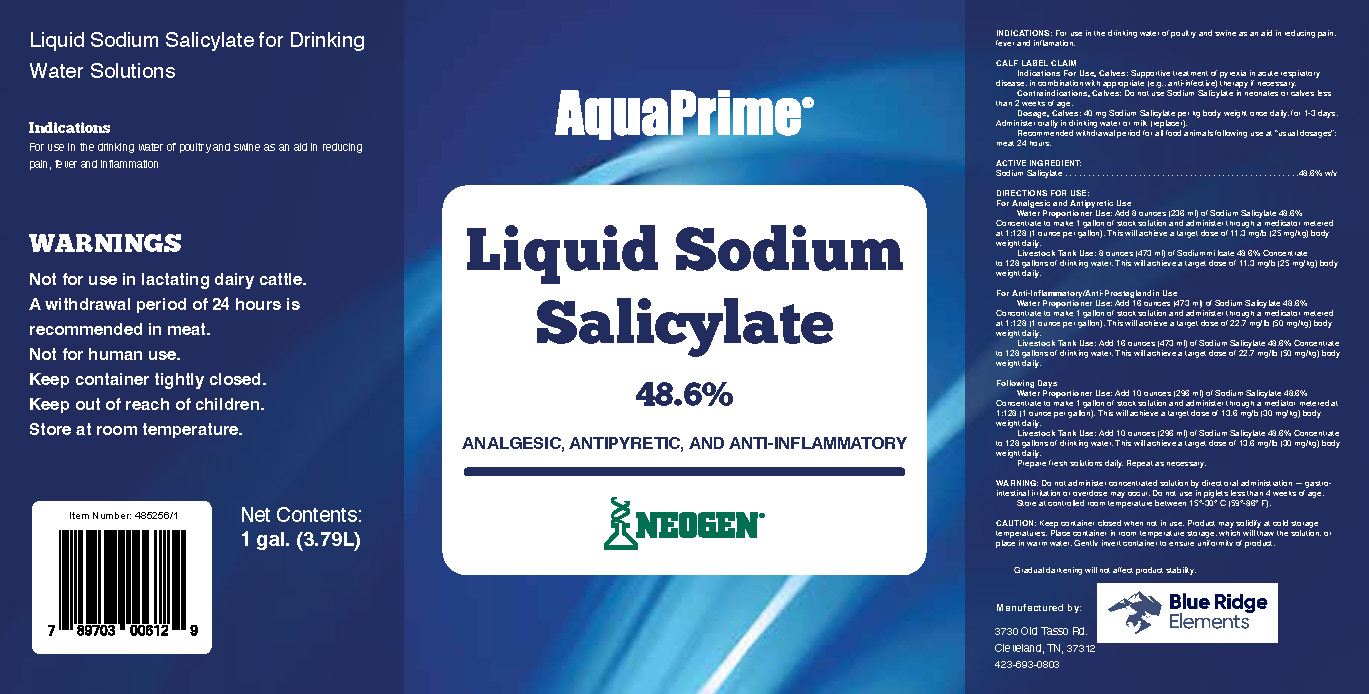 DRUG LABEL: AquaPrime Liquid Sodium Salicylate
NDC: 86050-2486 | Form: LIQUID
Manufacturer: Blendpack, Inc.
Category: animal | Type: OTC ANIMAL DRUG LABEL
Date: 20230728

ACTIVE INGREDIENTS: SODIUM SALICYLATE 486 g/1 L

AquaPrime Liquid Sodium Salicylate

Indications

For use in the drinking water of poultry and swine as an aid in reducing pain, fever and inflammation

CALF LABEL CLAIM

Indications For Use, Calves: Supportive treatment of pyrexia in acute respiratory disease, in combination with appropriate (e.g., anti-infective) therapy if necessary.

Contraindications, Calves: Do not use Sodium Salicylate in neonates or calves less than 2 weeks of age

Dosage, Calves: 40 mg Sodium Salicylate per kg body weight once daily, for 1-3 days. Administer orally in drinking water or milk (replacer).

Recommended withdrawal period for all food animals following use at “usual dosages”: meat 24 hours.

Warnings

Not for use in lactating dairy cattle.

A withdrawal period of 24 hours is recommended in meat.

Not for human use.

Keep container tightly closed.

Keep out of reach of children.

Store at room temperature.

Warning: Do not administer concentrated solution by direct oral administration — gastrointestinal irritation or overdose may occur. Do not use in piglets less than 4 weeks of age. Store at controlled room temperature between 15°-30° C (59°-86° F).

Directions for use

For Analgesic and Antipyretic Use
Water Proportioner Use: Add 8 ounces (236 ml) of Sodium Salicylate 48.6% Concentrate to make 1 gallon of stock solution and administer through a medicator metered at 1:128 (1 ounce per gallon). This will achieve a target dose of 11.3 mg/b (25 mg/kg) body weight daily.

Livestock Tank Use: 8 ounces (473 ml) of Sodium Salicylate 48 6% Concentrate to 128 gallons of drinking water. This will achieve a target dose of 11.3 mg/b (25 mg/kg) body weight daily.

For Anti-Inflammatory/Anti-Prostaglandin Use

Water Proportioner Use: Add 16 ounces (473 ml) of Sodium Salicylate 48.6% Concontrate to make 1 gallon of stock solution and administer through a medicator metered at 1:128 (1 ounce per gallon). This will achieve a target dose of 22.7 mg/lb (50 mg/kg) body weight daily.

Livestock Tank Use: Add 16 ounces (473 ml) of Sodium Salicylate 48.6% Concentrate to 128 gallons of drinking water. This will achieve a target dose of 22.7 mg/lb (50 mg/kg) body weight daily.

Following Days

Water Proportioner Use: Add 10 ounces (296 ml) of Sodium Salicylate 48.6% Concentrate to make 1 gallon of stock solution and administer through a mediator metered at 1:128 (1 ounce per gallon). This will achieve a target dose of 13.6 mg/b (30 mg/kg) body weight daily.

Livestock Tank Use: Add 10 ounces (296 ml) of Sodium Salicylate 48.6% Concentrate to 128 gallons of drinking water. This will achieve a target dose of 13.6 mg/lb (30 mg/kg) body weight daily.

Prepare fresh solutions daily. Repeat as necessary.

PACKAGE LABEL

Add image transcription here...